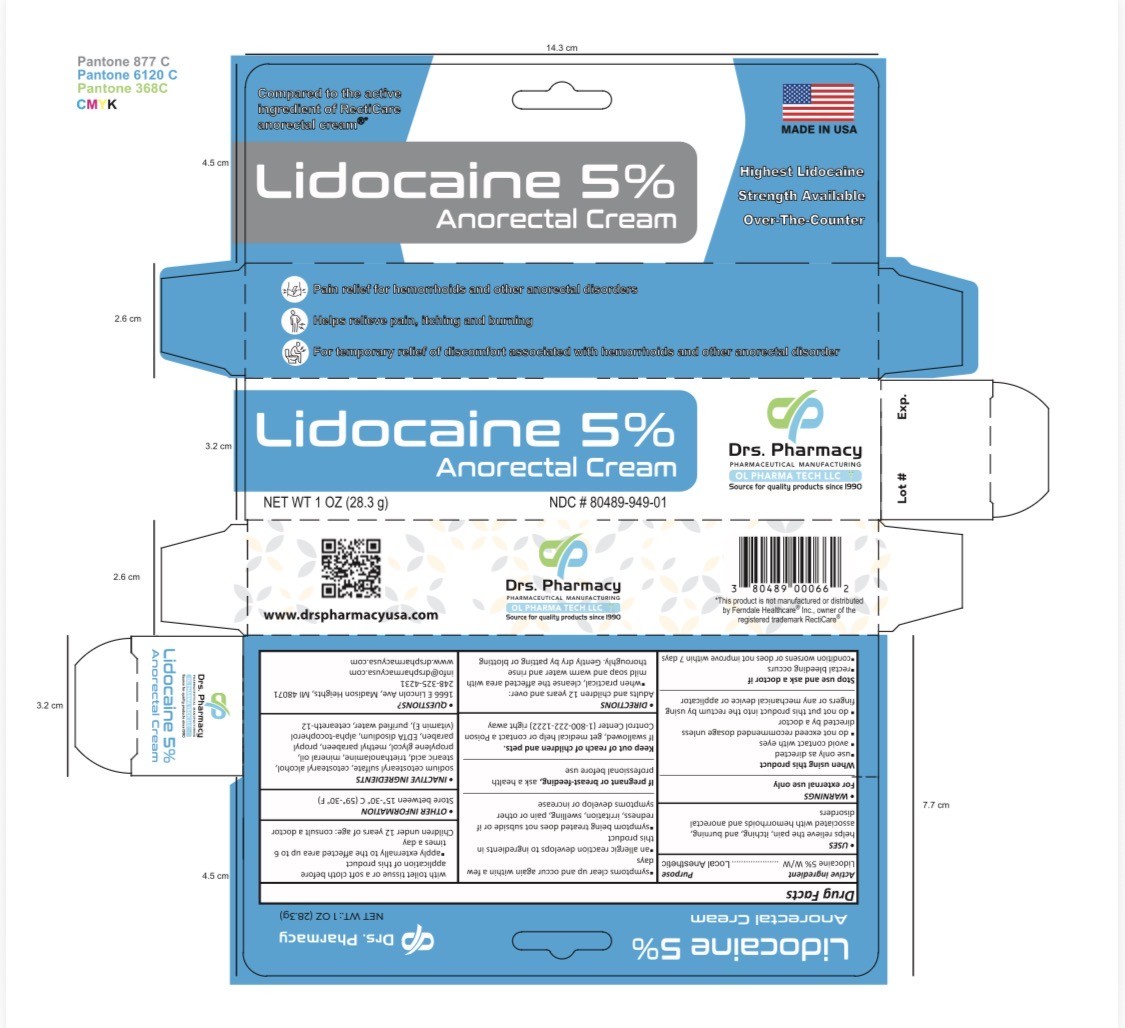 DRUG LABEL: Lidocaine cream
NDC: 80489-949 | Form: CREAM
Manufacturer: OL PHARMA TECH LLC. (Drs. Pharmacy)
Category: otc | Type: HUMAN OTC DRUG LABEL
Date: 20250609

ACTIVE INGREDIENTS: LIDOCAINE 5 g/100 g
INACTIVE INGREDIENTS: PROPYLPARABEN; CETOSTEARYL ALCOHOL; CETEARETH-12; TROLAMINE; PROPYLENE GLYCOL; METHYLPARABEN; EDETATE DISODIUM; WATER; MINERAL OIL; .ALPHA.-TOCOPHEROL; STEARIC ACID; SODIUM CETOSTEARYL SULFATE

ACTIVE INGREDIENT

LIDOCAINE 5%

PURPOSE

Topical anesthetic

USES

helps relieve the pain, itching, and burning, associated with hemorrhoids and anorectal disorders.

WARNINGS

- use only as directed.
- Avoid contact with eyes.
- do not exceed recommended dosage unless directed by a doctor.
- do not out this product into the rectum by using fingers or any mechanical device or applicator.

STOP USING AND ASK A DOCTOR IF:

- rectal bleeding occurs.
- condition worsens or does not improve within 7 days.
- symptoms clear up and occur again within a few days.
- an allergic reaction develops to ingredients in this product.
- symptom being treated does not subside or if redness, irritation, swelling, pain or other symptoms develop or increase.
- If pregnant or breast-feeding,ask a health professional before use.

keep out of reach of children and pets.If swallowed, get medical help or contact a Poison Control Center (1-800-222-1222) right away.

DIRECTIONS:

- Adult and children 12 years and over:

When practical, cleanse the affected area with mild soap and warm water and rinse thoroughly, gently dry by patting or blotting with toilet tissue or a soft cloth before application of this product. apply externally to the affected area up to 6 times a day

- children under 12 years of age: consult a doctor.

OTHER INFORMATION

Store between 15°-30° C (59°-30° F).

QUESTIONS

TELEPHONE NUMBER : 248 325 4231

INACTIVE INGREDIENT

water. stearic acid, vitamin E, EDTA, cetostearyl alcohol, sodium cetostearyl sulfate, trolamine, methylparaben, mineral oil, propylene glycol, propyl paraben